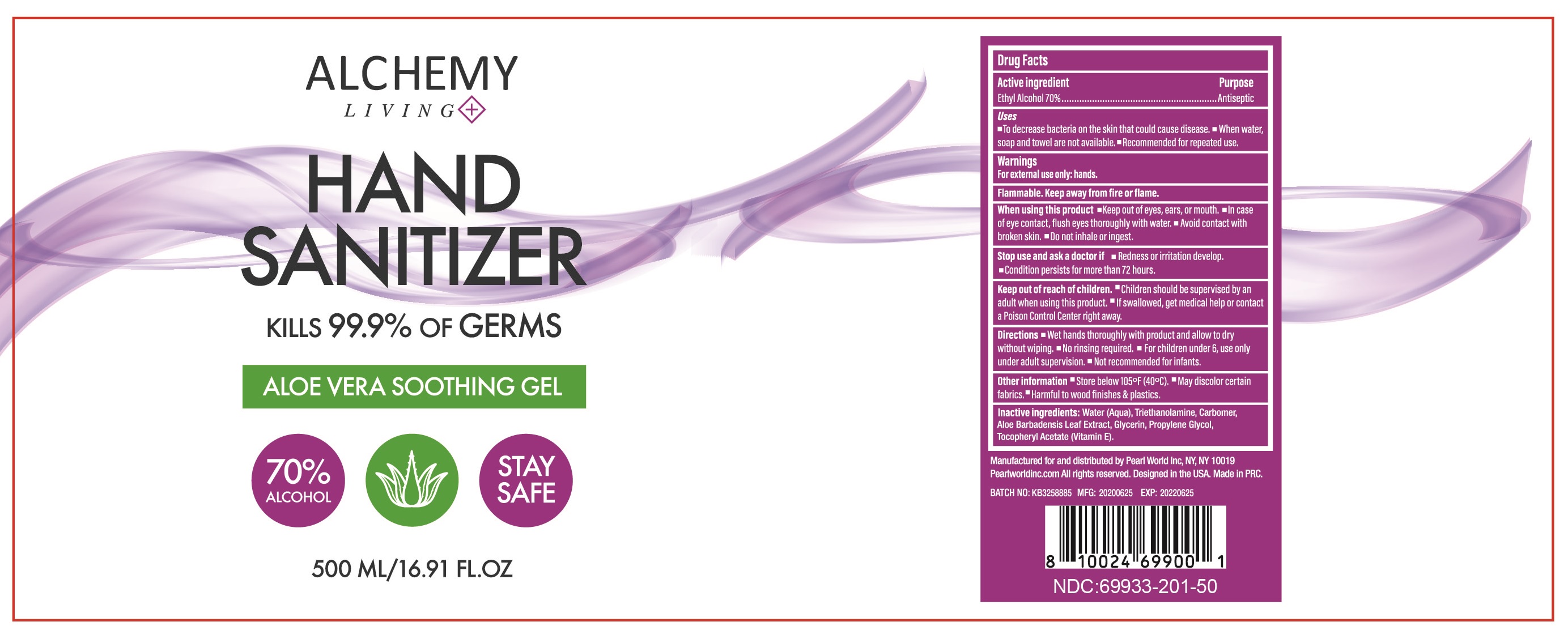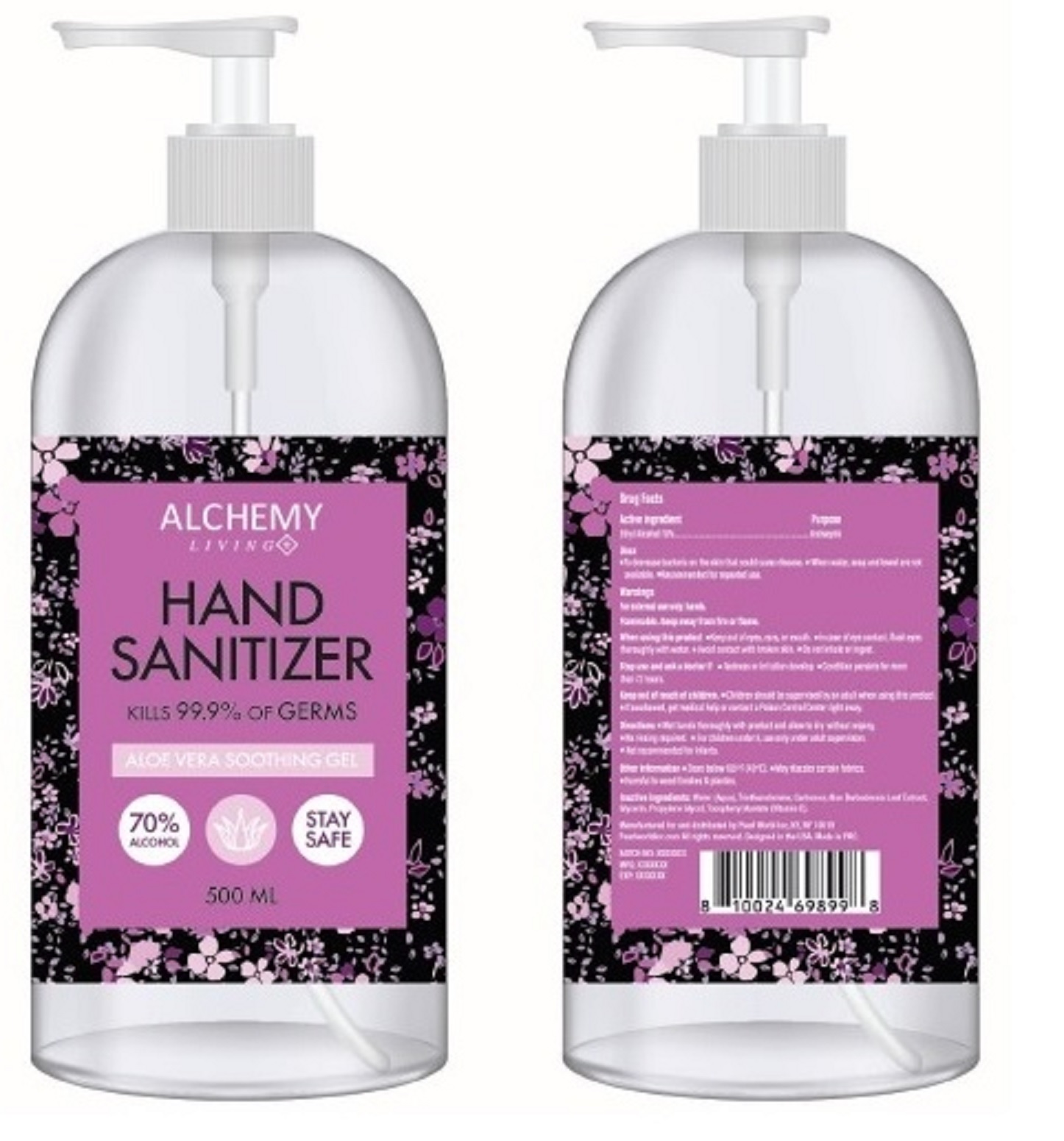 DRUG LABEL: Alchemy Living Hand Sanitizer
NDC: 69933-501 | Form: GEL
Manufacturer: PEARL WORLD INC.
Category: otc | Type: HUMAN OTC DRUG LABEL
Date: 20200714

ACTIVE INGREDIENTS: ALCOHOL 350 mL/500 mL
INACTIVE INGREDIENTS: ALOE VERA LEAF; CARBOMER HOMOPOLYMER, UNSPECIFIED TYPE; .ALPHA.-TOCOPHEROL ACETATE; PROPYLENE GLYCOL; WATER; GLYCERIN; TROLAMINE

69933-501 500ml 70%

Active Ingredient(s)

Ethyl Alcohol 70%

Purpose

Antiseptic

Use

■ To decrease bacteria on the skin that could cause disease.

■ When water, soap and towel are not available.

■ Recommended for repeated use.

Warnings

For external use only: hands.

Flammable. Keep away from fire or flame.

When using this product

■ Keep out of eyes, ears, or mouth.

■ In case of eye contact, flush eyes thoroughly with water.

■ Avoid contact with broken skin.

■ Do not inhale or ingest.

Stop use and ask a doctor if

■ Redness or irritation develop

■ Condition persists for more than 72 hours.

Keep out of reach of children.

■ Children should be supervised by an adult when using this product.

■ If swallowed, get medical help or contact a Poison Control Center right away.

Directions

■ Wet hands thoroughly with product and allow to dry without wiping.

■ No rinsing required.

■ For children under 6, use only under adult supervision.

■ Not recommended for infants.

Inactive ingredients

Inactive ingredients: Water (Aqua), Triethanolamine, Carbomer, Aloe Barbadensis Leaf Extract, Glycerin, Propylene Glycol, Tocopheryl Acetate (Vitamin E)

KILLS 99.9% OF GERMS

ALOE VERA SOOTHING GEL

70% ALCOHOL

STAY SAFE

Manufactured for and distributed by Pearl World Inc, NY, NY 10019 Pearlworldinc.com

All rights reserved. Designed in the USA. Made in PRC.

Other information

■ Store below 105°F (40°C).

■ May discolor certain fabrics.

■ Harmful to wood finishes & plastics.

KEEP OUT OF REACH OF CHILDREN

■ Children should be supervised by an adult when using this product.

■ If swallowed, get medical help or contact a Poison Control Center right away.

Package Label - Principal Display Panel

500 mL in 1 bottle NDC: 69933-501-01